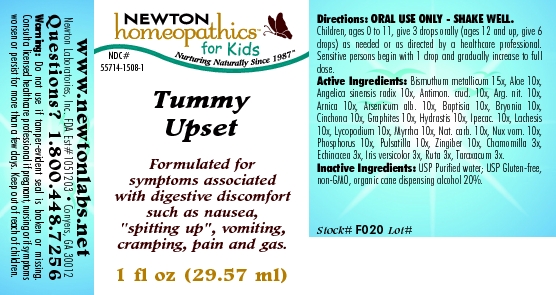 DRUG LABEL: Tummy Upset 
NDC: 55714-1508 | Form: LIQUID
Manufacturer: Newton Laboratories, Inc.
Category: homeopathic | Type: HUMAN OTC DRUG LABEL
Date: 20110301

ACTIVE INGREDIENTS: Bismuth 15 [hp_X]/1 mL; Aloe 10 [hp_X]/1 mL; Angelica Sinensis Root 10 [hp_X]/1 mL; Antimony Trisulfide 10 [hp_X]/1 mL; Silver Nitrate 10 [hp_X]/1 mL; Arnica Montana 10 [hp_X]/1 mL; Arsenic Trioxide 10 [hp_X]/1 mL; Baptisia Tinctoria 10 [hp_X]/1 mL; Bryonia Alba Root 10 [hp_X]/1 mL; Cinchona Officinalis Bark 10 [hp_X]/1 mL; Graphite 10 [hp_X]/1 mL; Goldenseal 10 [hp_X]/1 mL; Ipecac 10 [hp_X]/1 mL; Lachesis Muta Venom 10 [hp_X]/1 mL; Lycopodium Clavatum Spore 10 [hp_X]/1 mL; Myrrh 10 [hp_X]/1 mL; Sodium Carbonate 10 [hp_X]/1 mL; Strychnos Nux-vomica Seed 10 [hp_X]/1 mL; Phosphorus 10 [hp_X]/1 mL; Pulsatilla Vulgaris 10 [hp_X]/1 mL; Ginger 10 [hp_X]/1 mL; Matricaria Recutita 3 [hp_X]/1 mL; Echinacea, Unspecified 3 [hp_X]/1 mL; Iris Versicolor Root 3 [hp_X]/1 mL; Ruta Graveolens Flowering Top 3 [hp_X]/1 mL; Taraxacum Officinale 3 [hp_X]/1 mL
INACTIVE INGREDIENTS: Alcohol

Tummy Upset

INDICATIONS & USAGE SECTION

Tummy Upset Formulated for symptoms associated with digestive discomfort such as nausea, "spitting up", vomiting, cramping, pain and gas.

DOSAGE & ADMINISTRATION SECTION

ORAL USE ONLY - SHAKE WELL. Children, ages 0 to 11, give 3 drops orally (ages 12 and up, give 6 drops) as needed or as directed by a healthcare professional. Sensitive persons begin with 1 drop and gradually increase to full dose.

OTC - ACTIVE INGREDIENT SECTION

Bismuthum metallicum 15x, Aloe 10x, Angelica sinensis radix 10x, Antimon. crud. 10x, Arg. nit. 10x, Arnica 10x, Arsenicum alb. 10x, Baptisia 10x, Bryonia 10x, Cinchona 10x, Graphites 10x, Hydrastis 10x, Ipecac. 10x, Lachesis 10x, Lycopodium 10x, Myrrha 10x, Nat. carb. 10x, Nux vom. 10x, Phosphorus 10x, Pulsatilla 10x, Zingiber 10x, Chamomilla 3x, Echinacea 3x, Iris versicolor 3x, Ruta 3x, Taraxacum 3x.

OTC - PURPOSE SECTION

Formulated for symptoms associated with digestive discomfort such as nausea,"spitting up", vomiting, cramping, pain and gas.

INACTIVE INGREDIENT SECTION

Inactive Ingredients: USP Purified Water; USP Gluten-free, non-GMO, organic cane dispensing alcohol 20%.

QUESTIONS SECTION

www.newtonlabs.net Newton Laboratories, Inc. FDA Est # 1051203 - Conyers, GA 30012
Questions? 1.800.448.7256

WARNINGS SECTION

Warning: Do not use if tamper - evident seal is broken or missing. Consult a licensed healthcare professional if pregnant, nursing or if symptoms worsen or persist for more than a few days. Keep out of reach of children.

OTC - PREGNANCY OR BREAST FEEDING SECTION

Consult a licensed healthcare professional if pregnant, nursing or if symptoms worsen or persist for more than a few days.

OTC - KEEP OUT OF REACH OF CHILDREN SECTION

Keep out of reach of children.